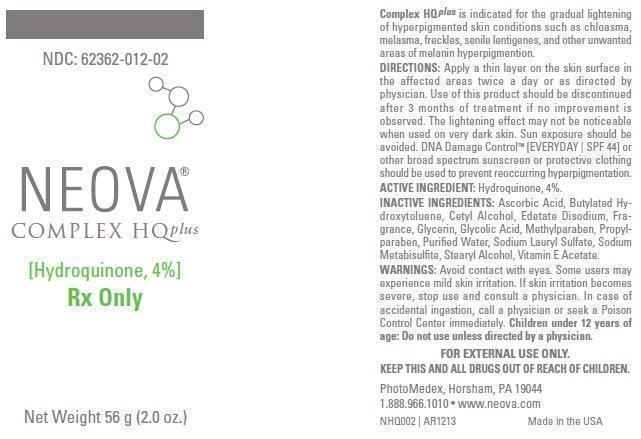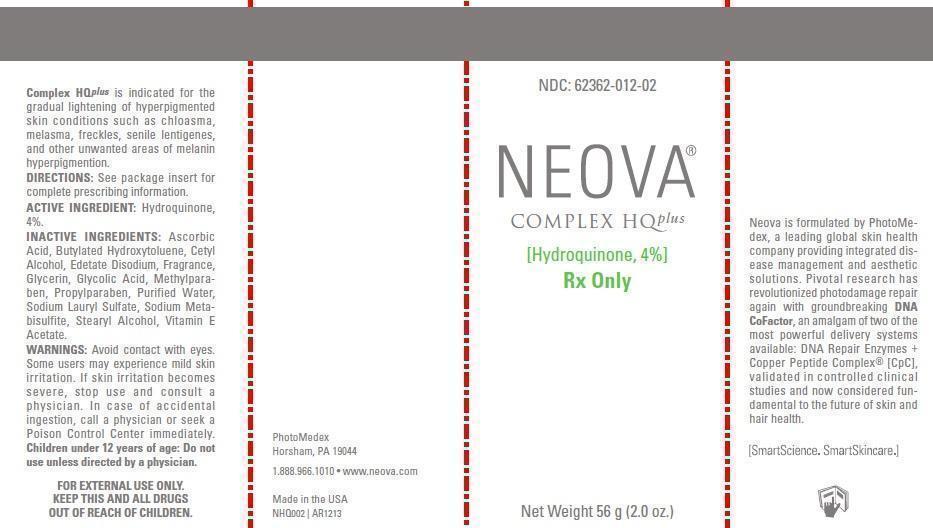 DRUG LABEL: Neova
NDC: 62362-012 | Form: EMULSION
Manufacturer: PhotoMedex, Inc.
Category: prescription | Type: HUMAN PRESCRIPTION DRUG LABEL
Date: 20140102

ACTIVE INGREDIENTS: HYDROQUINONE 40 mg/1 g
INACTIVE INGREDIENTS: ASCORBIC ACID; BUTYLATED HYDROXYTOLUENE; CETYL ALCOHOL; EDETATE DISODIUM; GLYCERIN; GLYCOLIC ACID; METHYLPARABEN; PROPYLPARABEN; WATER; SODIUM LAURYL SULFATE; SODIUM METABISULFITE; STEARYL ALCOHOL; .ALPHA.-TOCOPHEROL ACETATE

Neova Complex HQ Plus - Hydroquinone 4%

INDICATIONS AND USAGE

Complex HQ Plus is indicated for the gradual lightening of hyperpigmented skin conditions such as chloasma, melasma, freckles, senile lentigenes, and other unwanted areas of melanin hyperpigmention.

DIRECTIONS:

Apply a thin layer on the skin surface in the affected areas twice a day or as directed by physician. Use of this product should be discontinued after 3 months of treatment if no improvement is observed. The lightening effect may not be noticeable when used on very dark skin. Sun exposure should be avoided. DNA Damage Control [EVERYDAY BROAD SPECTRUM SPF 44] or other broad spectrum sunblock or protective clothing should be used to prevent reoccurring hyperpigmentation.

ACTIVE INGREDIENT:

Hydroquinone, 4%

INACTIVE INGREDIENTS:

Ascorbic Acid, Butylated Hydroxytoluene, Cetyl Alcohol, Edetate Disodium, Fragrance, Glycerin, Glycolic Acid, Methylparaben, Propylparaben, Purified Water, Sodium Lauryl Sulfate, Sodium Metabisulfite, Stearyl Alcohol, Vitamin E Acetate.

WARNINGS:

Avoid contact with eyes. Some users may experience mild skin irritation. If skin irritation becomes severe, stop use and consult a physician. In case of accidental ingestion, call a physician or seek a Poison Control Center immediately. Children under 12 years of age: Do not use unless directed by a physician.

KEEP OUT OF REACH OF CHILDREN

FOR EXTERNAL USE ONLY.

KEEP THIS AND ALL DRUGS OUT OF REACH OF CHILDREN.

PhotoMedex, Horsham, PA 19044
1.888.966.1010 • www.neova.com
Made in the USA

Neova Complex HQ Plus 2oz. (56.7 g) label and box

ComplexHQplus2ozLabel.jpg ComplexHQplusBox.jpg